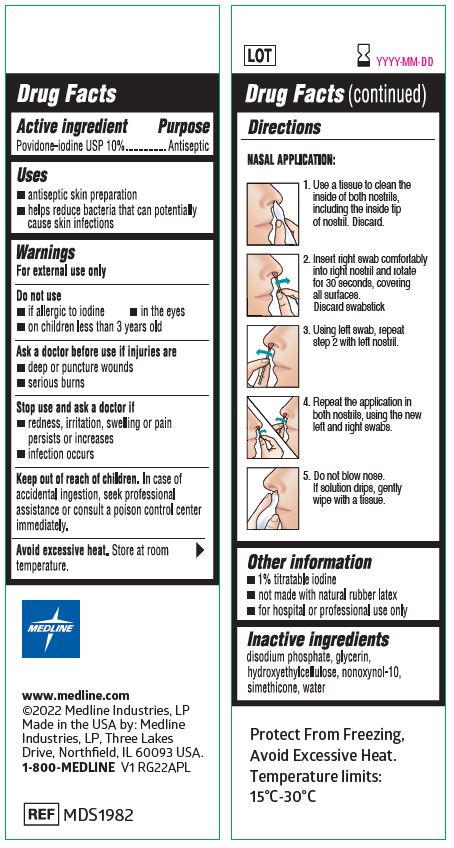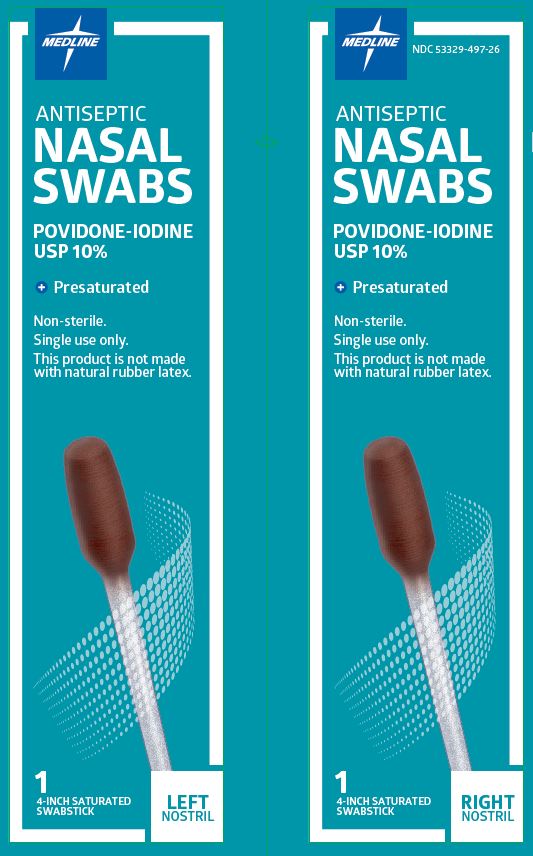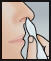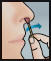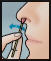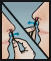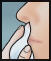 DRUG LABEL: 10% Povidone Iodine Nasal Swab
NDC: 83062-497 | Form: SOLUTION
Manufacturer: IIMED MEDICAL MEXICANA S DE RL DE CV
Category: otc | Type: HUMAN OTC DRUG LABEL
Date: 20240205

ACTIVE INGREDIENTS: POVIDONE-IODINE 10 mg/1 mL
INACTIVE INGREDIENTS: DIMETHICONE; SILICON DIOXIDE; SODIUM PHOSPHATE, DIBASIC, ANHYDROUS; HYDROXYETHYL CELLULOSE (2000 MPA.S AT 1%); NONOXYNOL-10; GLYCERIN; WATER

IIMED - 10% Povidone Iodine Nasal Swab

Active ingredient

Povidone-iodine USP 10%

Purpose

Antiseptic

Uses

- • antiseptic skin preparation
- • helps reduce bacteria that can potentially cause skin infections

Warnings

For external use only

Do not use

- • if allergic to iodine
- • in the eyes
- • on children less than 3 years old

Ask a doctor before use if injuries are

- • deep or puncture wounds
- • serious burns

Stop use and ask a doctor if

- • redness, irritation, swelling or pain persists or increases
- • infection occurs

Keep out of reach of children.

In case of accidental ingestion, seek professional assistance or consult a poison control center immediately.

STORAGE AND HANDLING

Avoid excessive heat.Store at room temperature.

Directions

NASAL APPLICATION:

- Use a tissue to clean the inside of both nostrils, including the inside tip of nostril. Discard.

- Insert swab comfortably into one nostril and rotate for 30 seconds, covering all surfaces. Discard swabstick.

- Using a 2nd swab, repeat step 2 with the other nostril.

- Repeat the application in both nostrils, using the 3rd and 4th swabs.

- Do not blow nose. If solution drips, gently wipe with a tissue.

Other information

- • 1% titratable iodine
- • not made with natural rubber latex
- • for hospital or professional use only

Inactive ingredients

disodium phosphate, glycerin, hydroxyethylcellulose, nonoxynol-10, simethicone, water